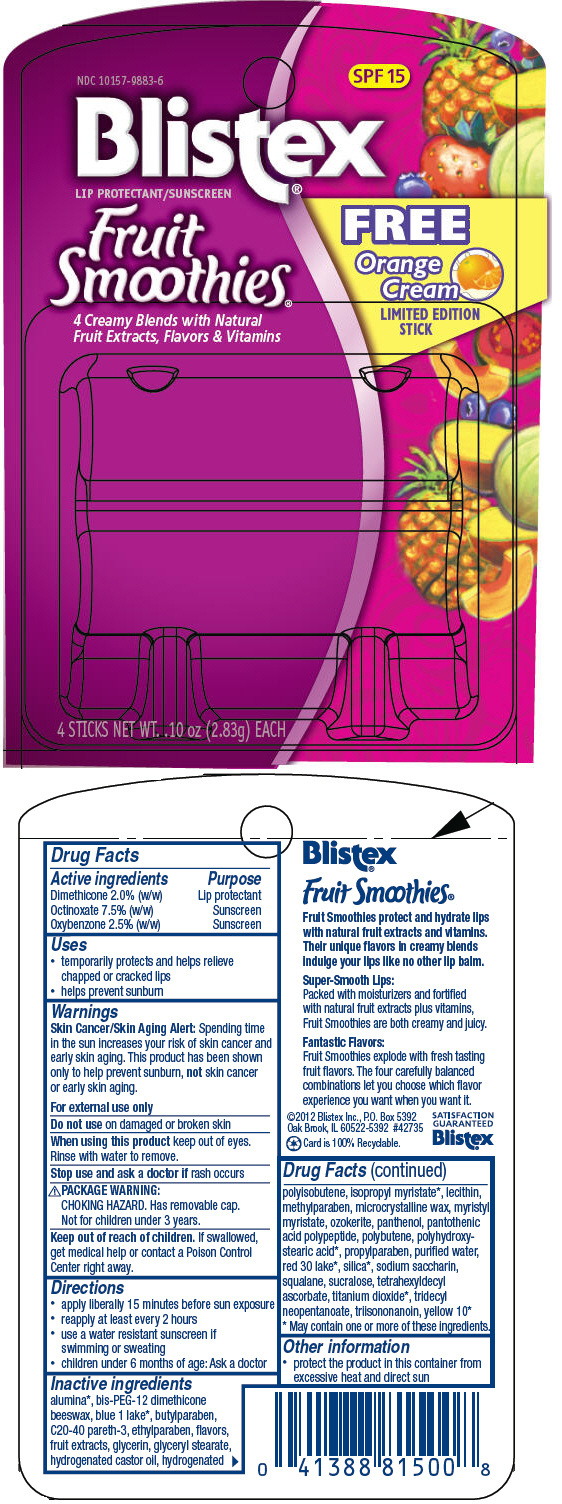 DRUG LABEL: Fruit Smoothies
NDC: 10157-9883 | Form: KIT | Route: TOPICAL
Manufacturer: Blistex Inc.
Category: otc | Type: HUMAN OTC DRUG LABEL
Date: 20130809

ACTIVE INGREDIENTS: Dimethicone 2 g/100 g; Octinoxate 7.5 g/100 g; Oxybenzone 2.5 g/100 g; Dimethicone 2 g/100 g; Octinoxate 7.5 g/100 g; Oxybenzone 2.5 g/100 g; Dimethicone 2 g/100 g; Octinoxate 7.5 g/100 g; Oxybenzone 2.5 g/100 g; Dimethicone 2 g/100 g; Octinoxate 7.5 g/100 g; Oxybenzone 2.5 g/100 g
INACTIVE INGREDIENTS: aluminum oxide; C20-40 pareth-3; glycerin; glyceryl monostearate; hydrogenated castor oil; isopropyl myristate; microcrystalline wax; myristyl myristate; panthenol; triisononanoin; silicon dioxide; saccharin sodium; squalane; sucralose; tetrahexyldecyl ascorbate; titanium dioxide; tridecyl neopentanoate; water; FD&C blue no. 1; D&C yellow no. 10; ceresin; propylparaben; butylparaben; ethylparaben; methylparaben; aluminum oxide; C20-40 pareth-3; glycerin; glyceryl monostearate; hydrogenated castor oil; isopropyl myristate; microcrystalline wax; myristyl myristate; panthenol; triisononanoin; silicon dioxide; saccharin sodium; squalane; sucralose; tetrahexyldecyl ascorbate; titanium dioxide; tridecyl neopentanoate; water; D&C red no. 30; D&C yellow no. 10; ceresin; propylparaben; butylparaben; ethylparaben; methylparaben; aluminum oxide; C20-40 pareth-3; glycerin; glyceryl monostearate; hydrogenated castor oil; isopropyl myristate; microcrystalline wax; myristyl myristate; panthenol; triisononanoin; silicon dioxide; saccharin sodium; squalane; sucralose; tetrahexyldecyl ascorbate; titanium dioxide; tridecyl neopentanoate; water; FD&C blue no. 1; D&C red no. 30; ceresin; propylparaben; butylparaben; ethylparaben; methylparaben; C20-40 pareth-3; glycerin; glyceryl monostearate; hydrogenated castor oil; microcrystalline wax; myristyl myristate; panthenol; triisononanoin; saccharin sodium; squalane; sucralose; tetrahexyldecyl ascorbate; tridecyl neopentanoate; water; ceresin; propylparaben; butylparaben; ethylparaben; methylparaben

Blistex (Fruit Smoothies)

Drug Facts

ACTIVE INGREDIENT

Active ingredients | Purpose
Dimethicone 2.0% (w/w) | Lip protectant
Octinoxate 7.5% (w/w) | Sunscreen
Oxybenzone 2.5% (w/w) | Sunscreen

Uses

- temporarily protects and helps relieve chapped or cracked lips
- helps prevent sunburn

Warnings

Skin Cancer/Skin Aging Alert

Spending time in the sun increases your risk of skin cancer and early skin aging. This product has been shown only to help prevent sunburn, not skin cancer or early skin aging.

For external use only

Do not use on damaged or broken skin

When using this product keep out of eyes. Rinse with water to remove.

Stop use and ask a doctor if rash occurs

PACKAGE WARNING

CHOKING HAZARD. Has removable cap. Not for children under 3 years.

Keep out of reach of children. If swallowed, get medical help or contact a Poison Control Center right away.

Directions

- apply liberally 15 minutes before sun exposure
- reapply at least every 2 hours
- use a water resistant sunscreen if swimming or sweating
- children under 6 months of age: Ask a doctor

Inactive ingredients

alumina [May contain one or more of these ingredients.] , bis-PEG-12 dimethicone beeswax, blue 1 lake, butylparaben, C20-40 pareth-3, ethylparaben, flavors, fruit extracts, glycerin, glyceryl stearate, hydrogenated castor oil, hydrogenated polyisobutene, isopropyl myristate, lecithin, methylparaben, microcrystalline wax, myristyl myristate, ozokerite, panthenol, pantothenic acid polypeptide, polybutene, polyhydroxystearic acid, propylparaben, purified water, red 30 lake, silica, sodium saccharin, squalane, sucralose, tetrahexyldecyl ascorbate, titanium dioxide, tridecyl neopentanoate, triisononanoin, yellow 10

Other information

- protect the product in this container from excessive heat and direct sun

PRINCIPAL DISPLAY PANEL - 4 Stick Blister Pack

NDC 10157-9883-6

SPF 15

Blistex®
LIP PROTECTANT/SUNSCREEN

Fruit
Smoothies®

4 Creamy Blends with Natural
Fruit Extracts, Flavors & Vitamins

FREE
Orange
Cream
LIMITED EDITION
STICK

4 STICKS NET WT. .10 oz (2.83g) EACH